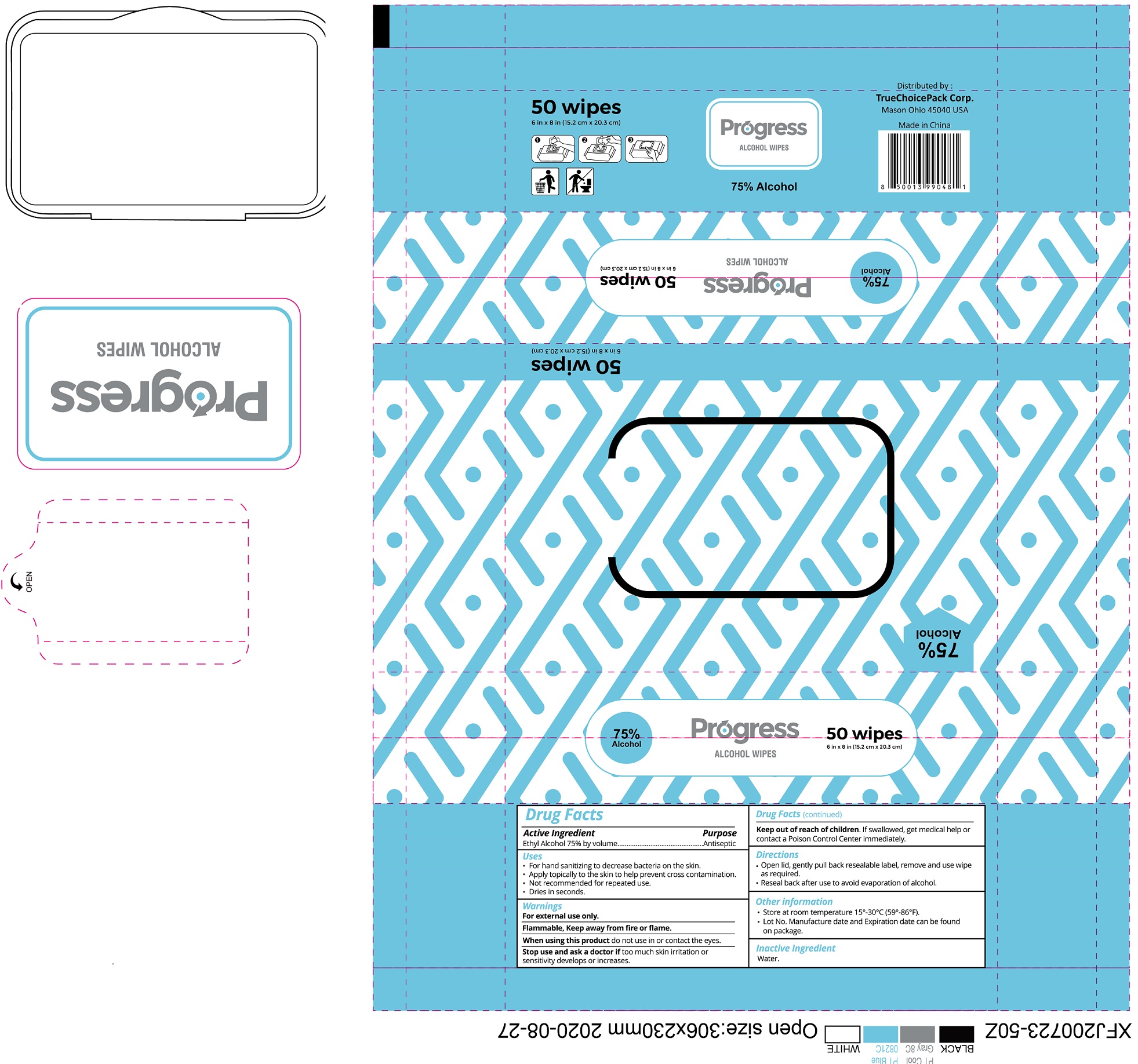 DRUG LABEL: Progress Alcohol Wipes
NDC: 80882-001 | Form: CLOTH
Manufacturer: Truechoicepack, Corp
Category: otc | Type: HUMAN OTC DRUG LABEL
Date: 20201026

ACTIVE INGREDIENTS: ALCOHOL 0.75 mL/1 mL
INACTIVE INGREDIENTS: WATER

Progress Alcohol Wipes

Active Ingredient

Ethyl Alcohol 75% by volume

Purpose

Antiseptic

Uses

- For hand washing to decrease bacteria on skin.
- Apply topically to the skin to help prevent cross contamination.
- Not recommended for repeated use.
- Dries in seconds.

Warnings

For external use only.
Flammable, Keep away from fire or flame.

When using this product

do not use in or contact the eyes.

Stop use and ask a doctor if

too much skin irritation or sensitivity develops or increases.

Keep out of reach of children.

If swallowed, get medical help or contact a Poison Control Center immediately.

Directions

- Open lid, gently pull back resealable label, remove and use wipe as required.
- Reseal back after use to avoid evaporation of alcohol.

Other information

- Store at room temperature 15°-30°C (59°-86°F).
- Lot No. Manufacture date and Expiration date can be found on package.

Inactive Ingredient

Water